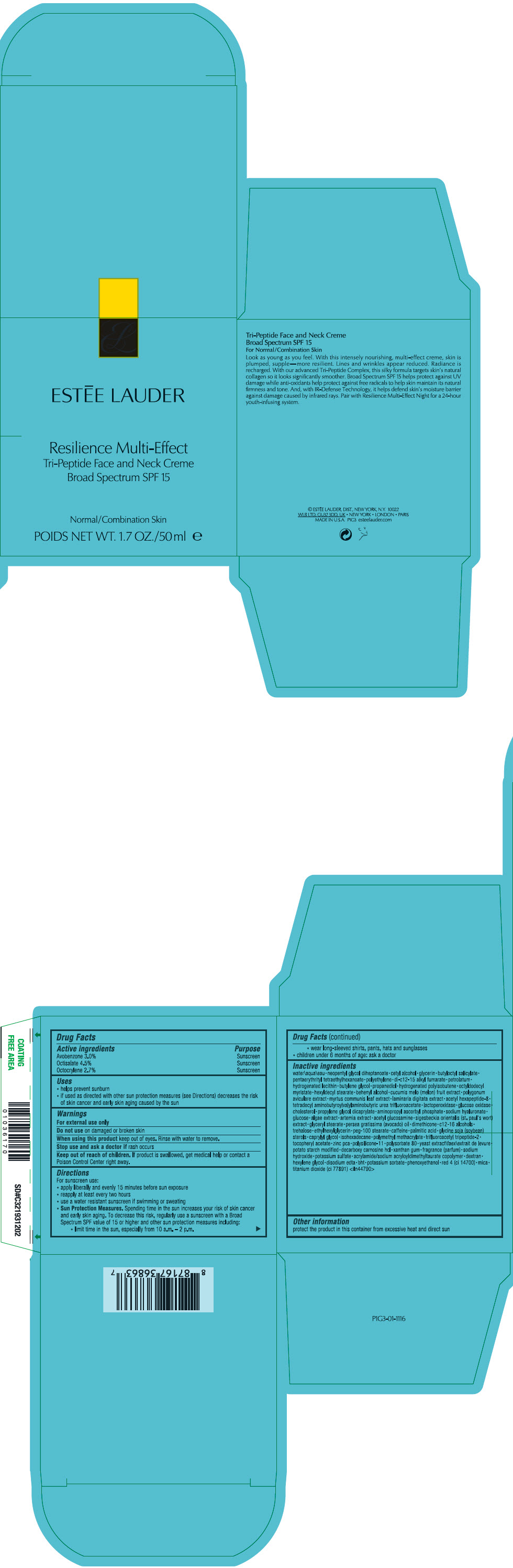 DRUG LABEL: RESILIENCE MULTI-EFFECT TRI-PEPTIDE FACE AND NECK CREME BROAD SPECTRUM SPF 15
NDC: 11559-052 | Form: CREAM
Manufacturer: ESTEE LAUDER INC
Category: otc | Type: HUMAN OTC DRUG LABEL
Date: 20250408

ACTIVE INGREDIENTS: AVOBENZONE 30 mg/1 mL; OCTISALATE 45 mg/1 mL; OCTOCRYLENE 27 mg/1 mL
INACTIVE INGREDIENTS: WATER; NEOPENTYL GLYCOL DIHEPTANOATE; CETYL ALCOHOL; GLYCERIN; BUTYLOCTYL SALICYLATE; PENTAERYTHRITYL TETRAETHYLHEXANOATE; HIGH DENSITY POLYETHYLENE; DI-C12-15 ALKYL FUMARATE; PETROLATUM; HYDROGENATED SOYBEAN LECITHIN; BUTYLENE GLYCOL; PROPANEDIOL; HYDROGENATED POLYBUTENE (1300 MW); OCTYLDODECYL MYRISTATE; HEXYLDECYL STEARATE; DOCOSANOL; MELON; ACETYL HEXAPEPTIDE-8; MYELOPEROXIDASE; GLUCOSE OXIDASE; CHOLESTEROL; PROPYLENE GLYCOL DICAPRYLATE; AMINOPROPYL ASCORBYL PHOSPHATE; HYALURONATE SODIUM; ANHYDROUS DEXTROSE; N-ACETYLGLUCOSAMINE; GLYCERYL MONOSTEARATE; AVOCADO; DIMETHICONE; C12-16 ALCOHOLS; TREHALOSE; ETHYLHEXYLGLYCERIN; PEG-100 STEARATE; CAFFEINE; PALMITIC ACID; SOY STEROL; CAPRYLYL GLYCOL; ISOHEXADECANE; POLY(METHYL METHACRYLATE; 450000 MW); ZINC PIDOLATE; POLYSORBATE 80; STARCH, POTATO; DECARBOXY CARNOSINE HYDROCHLORIDE; XANTHAN GUM; SODIUM HYDROXIDE; POTASSIUM SULFATE; HEXYLENE GLYCOL; EDETATE DISODIUM ANHYDROUS; BUTYLATED HYDROXYTOLUENE; POTASSIUM SORBATE; PHENOXYETHANOL; FD&C RED NO. 4; MICA; TITANIUM DIOXIDE

RESILIENCE MULTI-EFFECT TRI-PEPTIDE FACE AND NECK CRÈME BROAD SPECTRUM SPF 15

Drug Facts

ACTIVE INGREDIENT

Active ingredients | Purpose
Avobenzone 3.0% | Sunscreen
Octisalate 4.5% | Sunscreen
Octocrylene 2.7% | Sunscreen

Uses

- helps prevent sunburn
- if used as directed with other sun protection measures (see Directions) decreases the risk of skin cancer and early skin aging caused by the sun

Warnings

For external use only

Do not use on damaged or broken skin

When using this product keep out of eyes. Rinse with water to remove.

Stop use and ask a doctor if rash occurs

Keep out of reach of children. If product is swallowed, get medical help or contact a Poison Control Center right away.

Directions

For sunscreen use:

- apply liberally and evenly 15 minutes before sun exposure
- reapply at least every two hours
- use a water resistant sunscreen if swimming or sweating
- Sun Protection Measures. Spending time in the sun increases your risk of skin cancer and early skin aging. To decrease this risk, regularly use a sunscreen with a Broad Spectrum SPF value of 15 or higher and other sun protection measures including:
  - limit time in the sun, especially from 10 a.m. – 2 p.m.
  - wear long-sleeved shirts, pants, hats and sunglasses
- children under 6 months of age: ask a doctor

Inactive ingredients

water\aqua\eau • neopentyl glycol diheptanoate • cetyl alcohol • glycerin • butyloctyl salicylate • pentaerythrityl tetraethylhexanoate • polyethylene • di-c12-15 alkyl fumarate • petrolatum • hydrogenated lecithin • butylene glycol • propanediol • hydrogenated polyisobutene • octyldodecyl myristate • hexyldecyl stearate • behenyl alcohol • cucumis melo (melon) fruit extract • polygonum aviculare extract • myrtus communis leaf extract • laminaria digitata extract • acetyl hexapeptide-8 • tetradecyl aminobutyroylvalylaminobutyric urea trifluoroacetate • lactoperoxidase • glucose oxidase • cholesterol • propylene glycol dicaprylate • aminopropyl ascorbyl phosphate • sodium hyaluronate • glucose • algae extract • artemia extract • acetyl glucosamine • sigesbeckia orientalis (st. paul's wort) extract • glyceryl stearate • persea gratissima (avocado) oil • dimethicone • c12-16 alcohols • trehalose • ethylhexylglycerin • peg-100 stearate • caffeine • palmitic acid • glycine soja (soybean) sterols • caprylyl glycol • isohexadecane • polymethyl methacrylate • trifluoroacetyl tripeptide-2 • tocopheryl acetate • zinc pca • polysilicone-11 • polysorbate 80 • yeast extract\faex\extrait de levure • potato starch modified • decarboxy carnosine hcl • xanthan gum • fragrance (parfum) • sodium hydroxide • potassium sulfate • acrylamide/sodium acryloyldimethyltaurate copolymer • dextran • hexylene glycol • disodium edta • bht • potassium sorbate • phenoxyethanol • red 4 (ci 14700) • mica • titanium dioxide (ci 77891) <iln44790>

Other information

protect the product in this container from excessive heat and direct sun

PRINCIPAL DISPLAY PANEL - 50 ml Jar Carton

ESTĒE LAUDER

Resilience Multi-Effect
Tri-Peptide Face and Neck Creme
Broad Spectrum SPF 15

Normal/Combination Skin

NET WT. 1.7 OZ./50 ml e